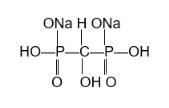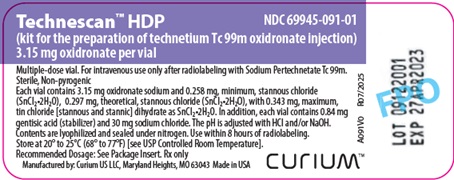 DRUG LABEL: Technescan HDP
NDC: 69945-091 | Form: INJECTION, POWDER, LYOPHILIZED, FOR SOLUTION
Manufacturer: Curium US LLC
Category: prescription | Type: HUMAN PRESCRIPTION DRUG LABEL
Date: 20251205

ACTIVE INGREDIENTS: OXIDRONATE DISODIUM 3.15 mg/1 1
INACTIVE INGREDIENTS: STANNOUS CHLORIDE; GENTISIC ACID; SODIUM CHLORIDE

Technescan™ HDP

(Kit for the Preparation of Technetium Tc 99m Oxidronate Injection)

For Intravenous Use

DESCRIPTION

Drug Characteristics

Technescan™ HDP (kit for the preparation of technetium Tc 99m oxidronate injection) is a radioactive diagnostic drug for intravenous use after radiolabeling with sodium pertechnetate Tc 99m injection.

Each vial contains 3.15 mg oxidronate sodium and 0.258 mg, minimum, stannous chloride (SnCl2•2H2O), 0.297 mg, theoretical, stannous chloride (SnCl2•2H2O) with 0.343 mg, maximum, tin chloride [stannous and stannic] dihydrate as SnCl2•2H2O, and the following inactive ingredients: 0.84 mg gentisic acid as a stabilizer and 30 mg sodium chloride. The pH is adjusted with hydrochloric acid and/or sodium hydroxide. The pH of the radiolabeled drug is between 4.0 and 5.5. The vial contains a sterile, non-pyrogenic, lyophilized powder packaged under nitrogen.

The chemical structure of oxidronate sodium is:

The structure of the technetium Tc 99m oxidronate complex is unknown.

Nuclear Physical Characteristics

Technetium-99m decays by isomeric transition with a physical half-life of 6.02 hours. The principal photon that is useful for detection and imaging is listed in Table 1.

Table 1. Principal Radiation Emission Data
Radiation | Mean % per Disintegration | Energy (keV)
Gamma-2 | 89.07 | 140.5

The specific gamma ray constant for technetium-99m is 0.795 R/hr-mCi at 1 cm. The first half-value layer is 0.023 cm of lead (Pb). A range of values for the relative attenuation of the radiation emitted by this radionuclide that results from interposition of various thicknesses of Pb is shown in Table 2. For example, the use of 0.27 cm of Pb will attenuate the external radiation emitted by a factor of about 1,000.

Table 2. Radiation Attenuation by Lead Shielding
Shield Thickness (Pb) cm | Coefficient of Attenuation
0.023 | 0.5
0.09 | 10^-1
0.18 | 10^-2
0.27 | 10^-3

To correct for physical decay of this radionuclide, the fractions that remain at selected time intervals after the time of calibration are shown in Table 3.

Table 3. Physical Decay Chart: Technetium-99m, Half-Life 6.02 Hours
Hours | Fraction Remaining | Hours | Fraction Remaining
0* | 1 | 7 | 0.447
1 | 0.891 | 8 | 0.398
2 | 0.794 | 9 | 0.355
3 | 0.708 | 10 | 0.316
4 | 0.631 | 11 | 0.282
5 | 0.562 | 12 | 0.251
6 | 0.501
* Calibration time

CLINICAL PHARMACOLOGY

During the 24 hours following injection, technetium Tc 99m oxidronate is cleared from blood and other non-osseous tissues and accumulates in the skeleton and urine in humans. Blood levels are about 10% of the injected dose at one hour post-injection and continue to fall to about 6%, 4% and 3% at 2, 3, and 4 hours, respectively. When measured at 24 hours following its administration, skeletal retention is approximately 50% of the injected dose. Technetium Tc 99m oxidronate exhibits its greatest affinity for areas of altered osteogenesis and actively metabolizing bone.

INDICATIONS AND USAGE

Technescan HDP, after radiolabeling with sodium pertechnetate Tc 99m, is indicated for skeletal imaging to demonstrate areas of altered osteogenesis in adult and pediatric patients.

CONTRAINDICATIONS

None known.

WARNINGS

Technetium Tc 99m oxidronate may cause life-threatening hypersensitivity reactions. Have cardiopulmonary resuscitation equipment and personnel available and monitor all patients for hypersensitivity reactions. (See ADVERSE REACTIONS.)

Technetium Tc 99m oxidronate is known to complex cations such as calcium. Particular caution should be used with patients who have or who may be predisposed to hypocalcemia.

The biodistribution of technetium Tc 99m oxidronate may be altered in the presence of high levels of certain cations (iron, calcium, and aluminum). This may result in reduced uptake of radionuclide in the skeleton and increased extraosseal uptake, which may potentially degrade imaging quality. High levels of these cations may be caused by concomitant medications or medical conditions (e.g., iron overload, hypercalcemia, etc.). Most cases were observed after iron infusion. (See PRECAUTIONS, Drug Interactions.)

PRECAUTIONS

General

Technetium Tc 99m oxidronate contributes to a patient’s overall long-term cumulative radiation exposure. Long-term cumulative radiation exposure is associated with an increased risk of cancer. Ensure safe drug handling to protect patients and healthcare providers from unintentional radiation exposure. (See DOSAGE AND ADMINISTRATION, Radiation Safety-Drug Handling.) To minimize radiation dose to the bladder, encourage patients to drink fluids before and after administration and to void immediately before the examination and as often thereafter as possible for the next 4 to 6 hours.

Drug Interactions

The biodistribution of technetium Tc 99m oxidronate may be altered in the presence of high levels of certain cations (iron, calcium, and aluminum). This may result in reduced uptake of radionuclide in the skeleton and increased extraosseal uptake, which may potentially degrade imaging quality. In patients with high levels of these cations caused by concomitant medications, particularly patients receiving iron infusions, consider performing an imaging study with technetium Tc 99m oxidronate injection once the cation levels have normalized (e.g., after 3 to 5 half-lives of the cation). (See WARNINGS.)

Carcinogenesis, Mutagenesis, Impairment of Fertility

No long-term animal studies have been performed to evaluate carcinogenic or mutagenic potential or whether technetium Tc 99m oxidronate affects fertility in males and females.

Pregnancy

Animal reproduction studies have not been conducted with technetium Tc 99m oxidronate. It is also not known whether technetium Tc 99m oxidronate can cause fetal harm when administered to a pregnant woman or can affect reproduction capacity.

All radiopharmaceuticals, including Tehnescan HDP, have the potential to cause fetal harm depending on the fetal stage of development and the magnitude of the radiation dose. If considering Technescan HDP administration to a pregnant woman, inform the patient about the potential for adverse pregnancy outcomes based on the radiation dose from technetium Tc 99m oxidronate and the gestational timing of exposure.

Nursing Mothers

Technetium-99m is excreted in human milk during lactation, therefore formula feedings should be substituted for breast feedings.

Pediatric Use

Technescan HDP, after radiolabeling with sodium pertechnetate Tc 99m, is indicated for skeletal imaging to demonstrate areas of altered osteogenesis in pediatric patients.

The relatively higher effective dose and radiation exposure of the epiphyses in growing bone should be considered in pediatric patients. (See DOSAGE AND ADMINISTRATION, Radiation Dosimetry).

Geriatric Use

This drug is known to be substantially excreted by the kidney, and the risk of toxic reactions to this drug may be greater in patients with impaired renal function. Because elderly patients are more likely to have decreased renal function, care should be taken in dose selection, and it may be useful to monitor renal function.

ADVERSE REACTIONS

The following adverse reactions associated with the use of Technescan HDP have been reported: hypersensitivity reactions, including life-threatening reactions, as well as nausea, vomiting, and injection site reactions.

OVERDOSAGE

In the event of the administration of an overdose of Technetium Tc 99m Oxidronate Injection, encourage patients to drink fluids and void frequently to reduce the radiation dose to the patient.

DOSAGE AND ADMINISTRATION

Radiation Safety – Drug Handling

After radiolabeling of Technescan HDP, the reaction vial contains Technetium Tc 99m Oxidronate Injection. Handle Technetium Tc 99m Oxidronate Injection with appropriate safety measures to minimize radiation exposure. (See PRECAUTIONS, General.) Use waterproof gloves, effective radiation shielding, and other appropriate safety measures when preparing and handling Technetium Tc 99m Oxidronate Injection.

Radiopharmaceuticals should be used by or under the control of healthcare providers who are qualified by specific training and experience in the safe use and handling of radionuclides, and whose experience and training have been approved by the appropriate governmental agency authorized to license the use of radionuclides.

Recommended Dosage

Adults

The recommended amount of radioactivity of Technetium Tc 99m Oxidronate Injection in adults is 555 MBq (15 mCi) with a range of 370 MBq to 740 MBq (10 mCi to 20 mCi).

The maximum dose of oxidronate sodium in adults is 2 mg.

Pediatric Patients

The recommended amount of radioactivity of Technetium Tc 99m Oxidronate Injection in pediatric patients is 7.4 MBq/kg to 13 MBq/kg (0.20 mCi/kg to 0.35 mCi/kg).

The recommended minimum and maximum activity in pediatric patients are 37 MBq (1 mCi) and 740 MBq (20 mCi), respectively. The maximum dose of oxidronate sodium in pediatric patients is 2 mg.

Administration Instructions

- Measure the patient dose with a dose calibrator just prior to administration.
- Administer the dose intravenously by slow injection 1 hour to 4 hours before imaging.
- To minimize radiation dose to the bladder, encourage the patients to drink fluids before and after administration of Technetium Tc 99m Oxidronate Injection and to void immediately before the examination and as often thereafter as possible for the next 6 hours. (See PRECAUTIONS, General.)

Directions for Drug Preparation

Procedural Precautions

- The contents of the vial are intended only for use in the preparation of Technetium Tc 99m Oxidronate Injection and are NOT to be administered directly to the patient.
- The components of the kit are sterile and non-pyrogenic. Follow the directions carefully and adhere to strict aseptic procedures during preparation.
- Sodium pertechnetate Tc 99m injection that contains an oxidizing agent or 0.9% sodium chloride injection containing preservatives is not suitable for use in the preparation of Technetium Tc 99m Oxidronate Injection.
- Wear waterproof gloves during the entire preparation procedure and during subsequent patient dose withdrawals from the reaction vial.
- Make all transfers of sodium pertechnetate Tc 99m injection using an adequately shielded syringe.
- Keep the prepared Technetium Tc 99m Oxidronate Injection in the lead vial shield with fitted lead cover in place during the useful life of the radioactive preparation. Make all withdrawals and injection of the Technetium Tc 99m Oxidronate Injection with an adequately shielded syringe.
- If the dose is for a single adult patient or for pediatric patients, see Directions for the Preparation of a Single Adult Dose or Pediatric Dose(s).

Directions for the Preparation of Adult Doses

1. Remove the plastic disc from the Technescan HDP vial and swab the rubber septum with an alcohol swab or a suitable bacteriostatic agent to disinfect the surface.
2. Place the vial in a lead vial shield. Add 3 mL to 6 mL of sodium pertechnetate Tc 99m injection and secure with a fitted lead cover. In choosing the amount of sodium pertechnetate Tc 99m injection radioactivity to be used, the number of doses desired, the activity of each dose, and radioactive decay must be taken into account. The recommended maximum activity of sodium pertechnetate Tc 99m injection to be added to the vial is 11,100 MBq (300 mCi).
3. Shake the vial gently, for approximately 30 seconds, to ensure complete dissolution.
4. Using proper shielding, visually inspect the reaction vial. The resulting solution should be clear and free of particulate matter. If not, do not use the product.
5. Assay the product in a suitable dose calibrator and record the time, date of preparation, and the activity of the Technetium Tc 99m Oxidronate Injection on the radioassay information label and affix it to the vial.
6. Determine the radiochemical purity prior to administration.
7. Store the reaction vial upright in the lead vial shield with fitted lead cover in place at room temperature, 20°C to 25°C (68° to 77°F). Use within 8 hours of radiolabeling.
8. Dispose of unused material in a safe manner in accordance with applicable regulations.

Directions for the Preparation of a Single Adult Dose or Pediatric Dose(s)

a. Remove the plastic cap from the Technescan HDP vial and swab the rubber septum with an alcohol swab or a suitable bacteriostatic agent to disinfect the surface.

b. Add 3 mL to 6 mL of 0.9% sodium chloride injection. Shake the vial gently for approximately 30 seconds to assure complete dissolution.

c. Withdraw and discard all but approximately 1 mL of the solution.

d. Place the vial in a lead vial shield. Add an appropriate amount of sodium pertechnetate Tc 99m injection for a single adult dose or for one or more pediatric doses and shake gently. No more than 1,480 MBq (40 mCi) should be added to the vial when preparing multiple pediatric doses.

e. Proceed with steps 4 through 8 above.

Radiation Dosimetry

Estimated absorbed radiation doses from an intravenous injection of Technetium Tc 99m Oxidronate Injection are shown in Table 4.

Table 4. Estimated Absorbed Radiation Doses in Organs and Tissues in Patients Who Received Technetium Tc 99m Oxidronate Injection
Organ/Tissue | Absorbed Dose* per Unit Activity Administered (mGy/MBq)
 | Adults | 15 years | 10 years | 5 years | 1 year
Adrenals | 0.0021 | 0.0026 | 0.0038 | 0.0058 | 0.0110
Bone surfaces | 0.0340 | 0.0150 | 0.0230 | 0.0380 | 0.0820
Brain | 0.0017 | 0.0020 | 0.0028 | 0.0042 | 0.0059
Breast | 0.0007 | 0.0009 | 0.0013 | 0.0021 | 0.0040
Gallbladder wall | 0.0014 | 0.0018 | 0.0033 | 0.0043 | 0.0065
GI tract
Stomach | 0.0012 | 0.0014 | 0.0024 | 0.0036 | 0.0064
Small intestine wall | 0.0022 | 0.0028 | 0.0043 | 0.0061 | 0.0093
Colon wall | 0.0027 | 0.0034 | 0.0052 | 0.0072 | 0.0100
Upper large intestine wall | 0.0019 | 0.0024 | 0.0038 | 0.0057 | 0.0087
Lower large intestine wall | 0.0038 | 0.0047 | 0.0071 | 0.0092 | 0.0130
Heart | 0.0012 | 0.0015 | 0.0022 | 0.0033 | 0.0059
Kidneys | 0.0072 | 0.0087 | 0.0120 | 0.0180 | 0.0310
Liver | 0.0012 | 0.0016 | 0.0024 | 0.0036 | 0.0064
Lungs | 0.0012 | 0.0016 | 0.0023 | 0.0035 | 0.0067
Muscles | 0.0018 | 0.0022 | 0.0033 | 0.0047 | 0.0077
Esophagus | 0.0010 | 0.0013 | 0.0019 | 0.0029 | 0.0051
Ovaries | 0.0036 | 0.0045 | 0.0065 | 0.0086 | 0.0120
Pancreas | 0.0016 | 0.0020 | 0.0030 | 0.0045 | 0.0079
Red marrow | 0.0059 | 0.0054 | 0.0088 | 0.0170 | 0.0360
Skin | 0.0010 | 0.0013 | 0.0019 | 0.0030 | 0.0053
Spleen | 0.0014 | 0.0018 | 0.0027 | 0.0044 | 0.0077
Testes | 0.0024 | 0.0033 | 0.0054 | 0.0085 | 0.0100
Thymus | 0.0010 | 0.0013 | 0.0019 | 0.0029 | 0.0051
Thyroid | 0.0013 | 0.0015 | 0.0022 | 0.0034 | 0.0054
Urinary bladder wall | 0.0470 | 0.0590 | 0.0870 | 0.1100 | 0.1300
Uterus | 0.0062 | 0.0075 | 0.0110 | 0.0140 | 0.0180
Remaining organs | 0.0019 | 0.0023 | 0.0034 | 0.0050 | 0.0077
Effective Dose (mSv/MBq) | 0.0049 | 0.0057 | 0.0086 | 0.0120 | 0.0180
*For normal skeletal uptake and kidney function

HOW SUPPLIED

Technescan HDP (kit for the preparation of technetium Tc 99m oxidronate injection) contains 3.15 mg oxidronate sodium as a white lyophilized powder in a multiple-dose vial.

Technescan HDP is available as:

• 5 vials per carton (NDC 69945-091-20)
• 30 vials per carton (NDC 69945-091-40)

Before radiolabeling, store at 20°C to 25°C (68°F to 77°F) [see USP Controlled Room Temperature].

After radiolabeling, store vial upright in appropriate shielding at 20°C to 25°C (68°F to 77°F) [see USP Controlled Room Temperature]. Use within 8 hours of radiolabeling.

Dispose of unused products in accordance with appropriate regulations.

This reagent kit is for distribution to persons licensed by the U.S. Nuclear Regulatory Commission or the relevant regulatory authority of an Agreement State.

Manufactured by: Curium US LLC

2703 Wagner Place

Maryland Heights, MO 63043

Made in USA

©2025 Curium US LLC. Technescan™, Curium™, and the Curium logo are trademarks of a Curium company.

A091I0

Revised: 11/2025

PRINCIPAL DISPLAY PANEL

Technescan™ HDP NDC 69945-091-01

(kit for the preparation of technetium Tc 99m oxidronate injection)

3.15 mg oxidronate per vial

Multiple-dose vial. For intravenous use only after radiolabeling with Sodium Pertechnetate Tc 99m.
Sterile, Non-pyrogenic

Each vial contains 3.15 mg oxidronate sodium and 0.258 mg, minimum, stannous chloride (SnCl2 ● 2H2O), 0.297 mg, theoretical, stannous chloride (SnCl2 ● 2H2O), with 0.343 mg, maximum, tin chloride [stannous and stannic] dihydrate as SnCl2 ● 2H2O. In addition, each vial contains 0.84 mg gentisic acid (stabilizer) and 30 mg sodium chloride. The pH is adjusted with HCl and/or NaOH. Contents are lyophilized and sealed under nitrogen. Use within 8 hours of radiolabeling.

Store at 20° to 25°C (68° to 77°F) [see USP Controlled Room Temperature].
Recommended Dosage: See Package Insert. Rx only

Manufactured by: Curium US LLC, Maryland Heights, MO 63043

Made in USA
CURIUM™

A091V0
R07/2025